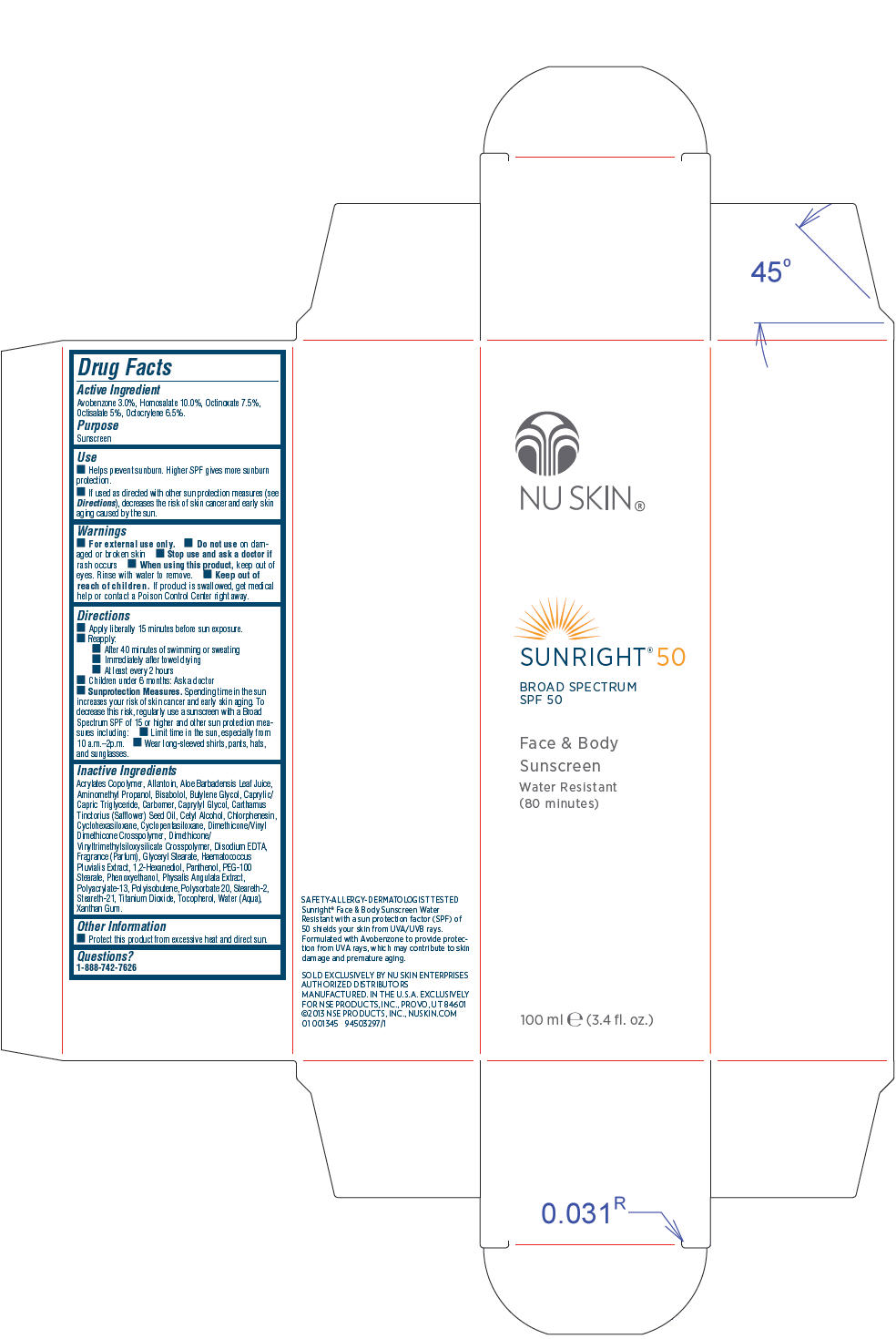 DRUG LABEL: Nu Skin Sunright 50 Broad Spectrum SPF 50
NDC: 62839-1345 | Form: LOTION
Manufacturer: NSE Products, Inc.
Category: otc | Type: HUMAN OTC DRUG LABEL
Date: 20191227

ACTIVE INGREDIENTS: Avobenzone 30 mg/1 mL; Homosalate 100 mg/1 mL; Octinoxate 75 mg/1 mL; Octisalate 50 mg/1 mL; Octocrylene 65 mg/1 mL
INACTIVE INGREDIENTS: Allantoin; Aloe Vera Leaf; Aminomethylpropanol; Levomenol; Butylene Glycol; Medium-Chain Triglycerides; Caprylyl Glycol; Safflower Oil; Cetyl Alcohol; Chlorphenesin; Cyclomethicone 6; Cyclomethicone 5; Edetate Disodium; Glyceryl Monostearate; Haematococcus Pluvialis; 1,2-Hexanediol; Panthenol; PEG-100 Stearate; Phenoxyethanol; Physalis Angulata; Steareth-2; Steareth-21; Polysorbate 20; Titanium Dioxide; Tocopherol; Water; Xanthan Gum

Nu Skin® Sunright® 50 Broad Spectrum SPF 50

Drug Facts

Active Ingredient

Avobenzone 3.0%, Homosalate 10.0%, Octinoxate 7.5%, Octisalate 5%, Octocrylene 6.5%.

Purpose

Sunscreen

Use

- Helps prevent sunburn. Higher SPF gives more sunburn protection.
- If used as directed with other sun protection measures (see Directions), decreases the risk of skin cancer and early skin aging caused by the sun.

Warnings

- For external use only.

- Do not use on damaged or broken skin

- Stop use and ask a doctor if rash occurs

- When using this product, keep out of eyes. Rinse with water to remove.

- Keep out of reach of children. If product is swallowed, get medical help or contact a Poison Control Center right away.

Directions

- Apply liberally 15 minutes before sun exposure.
- Reapply:
  - After 40 minutes of swimming or sweating
  - Immediately after towel drying
  - At least every 2 hours
- Children under 6 months: Ask a doctor
- Sunprotection Measures. Spending time in the sun increases your risk of skin cancer and early skin aging. To decrease this risk, regularly use a sunscreen with a Broad Spectrum SPF of 15 or higher and other sun protection measures including:
  - Limit time in the sun, especially from 10 a.m.–2p.m.
  - Wear long-sleeved shirts, pants, hats, and sunglasses.

Inactive Ingredients

Acrylates Copolymer, Allantoin, Aloe Barbadensis Leaf Juice, Aminomethyl Propanol, Bisabolol, Butylene Glycol, Caprylic/Capric Triglyceride, Carbomer, Caprylyl Glycol, Carthamus Tinctorius (Safflower) Seed Oil, Cetyl Alcohol, Chlorphenesin, Cyclohexasiloxane, Cyclopentasiloxane, Dimethicone/Vinyl Dimethicone Crosspolymer, Dimethicone/Vinyltrimethylsiloxysilicate Crosspolymer, Disodium EDTA, Fragrance (Parfum), Glyceryl Stearate, Haematococcus Pluvialis Extract, 1,2-Hexanediol, Panthenol, PEG-100 Stearate, Phenoxyethanol, Physalis Angulata Extract, Polyacrylate-13, Polyisobutene, Polysorbate 20, Steareth-2, Steareth-21, Titanium Dioxide, Tocopherol, Water (Aqua), Xanthan Gum.

Other Information

- Protect this product from excessive heat and direct sun.

Questions?

1-888-742-7626

PRINCIPAL DISPLAY PANEL - 100 mL Bottle Carton

NU SKIN®

SUNRIGHT® 50

BROAD SPECTRUM
SPF 50

Face & Body
Sunscreen

Water Resistant
(80 minutes)

100 ml e (3.4 fl. oz.)